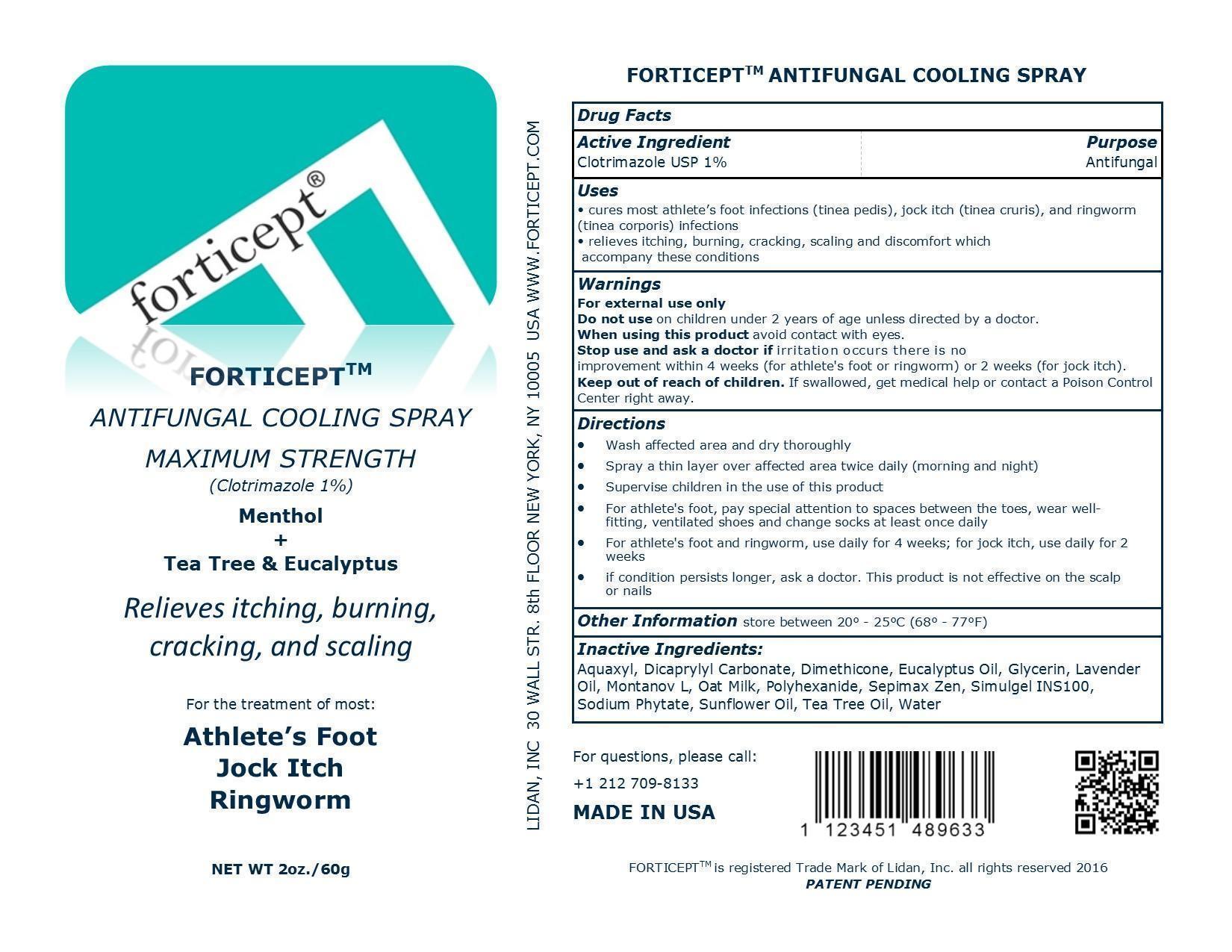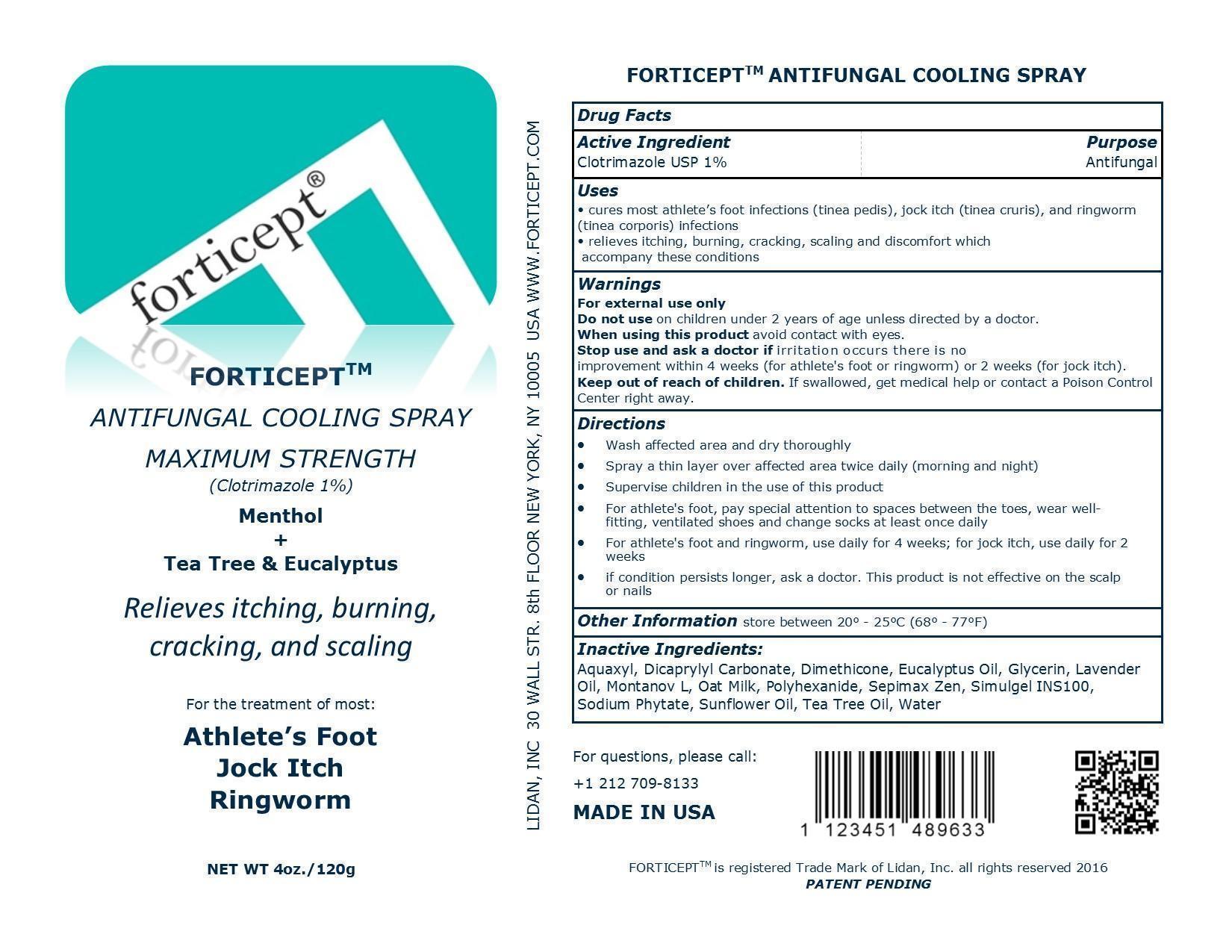 DRUG LABEL: Forticept Antifungal Cooling
NDC: 52261-0502 | Form: liquid
Manufacturer: Cosco International, Inc.
Category: otc | Type: HUMAN OTC DRUG LABEL
Date: 20160504

ACTIVE INGREDIENTS: CLOTRIMAZOLE 10 g/1000 g
INACTIVE INGREDIENTS: water 858.5 g/1000 g; glycerin 20 g/1000 g; dimethicone 20 g/1000 g; oat 15 g/1000 g; C14-22 Alcohols 15 g/1000 g; DICAPRYLYL CARBONATE 10 g/1000 g; sunflower oil 10 g/1000 g; polydextrose 10 g/1000 g; polihexanide hydrochloride 10 g/1000 g; HYDROXYETHYL ACRYLATE/SODIUM ACRYLOYLDIMETHYL TAURATE COPOLYMER (45000 MPA.s at 1%) 3.4 g/1000 g; isohexadecane 3.3 g/1000 g; polysorbate 60 3.3 g/1000 g; lavender oil 3 g/1000 g; CARBOXYPOLYMETHYLENE 3 g/1000 g; PHYTATE SODIUM 2 g/1000 g; eucalyptus oil 2 g/1000 g; Tea Tree oil 1.5 g/1000 g

Drug Facts

Active Ingredient/Purpose

Clotrimazole USP 1%........................Antifungal

Uses

- cures most athlete’s foot infections (tinea pedis), jock itch (tinea cruris), and ringworm (tinea corporis) infections
- relieves itching, burning, cracking, scaling and discomfort which accompany these conditions

Warnings

For external use only

Do not use on children under 2 years of age unless direceted by a doctor.

When using this product avoid contact with eyes.

Stop use and ask a doctor if irritation occurs or there is no improvement within 4 weeks (for athlete's foot or ringworm) or 2 weeks (for jock itch).

Keep out of reach of children. If swallowed, get medical help or contact a Poison Control Center right away.

Directions

- Wash affected area and dry thoroughly
- Spray a thin layer over affected area twice daily (morning and night)
- Supervise children in the use of this product
- For athlete's foot, pay special attention to spaces between the toes, wear well-fitting, ventilated shoes and change socks at least once daily
- For athlete's foot and ringworm, use daily for 4 weeks; for jock itch, use daily for 2 weeks
- if condition persists longer, ask a doctor. This product is not effective on the scalp or nails

Other Information store between 20° - 25°C (68° - 77°F)

Inactive ingredients:

Aquaxyl, Dicaprylyl Carbonate, Dimethicone, Eucalyptus Oil, Glycerin, Lavender Oil, Montanov L, Oat Milk, Polyhexanide, Sepimax Zen, Simulgel INS100, Sodium Phytate, Sunflower Oil, Tea Tree Oil, Water